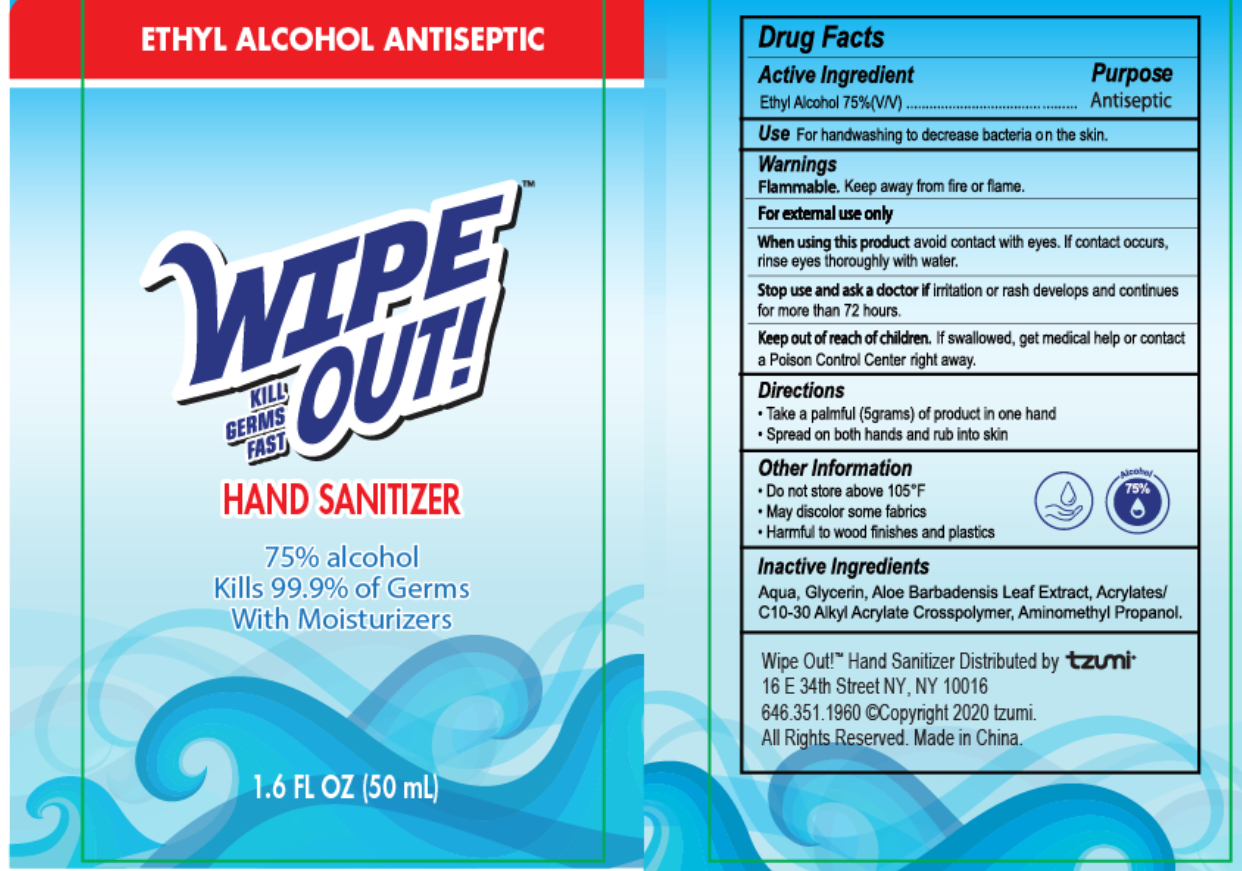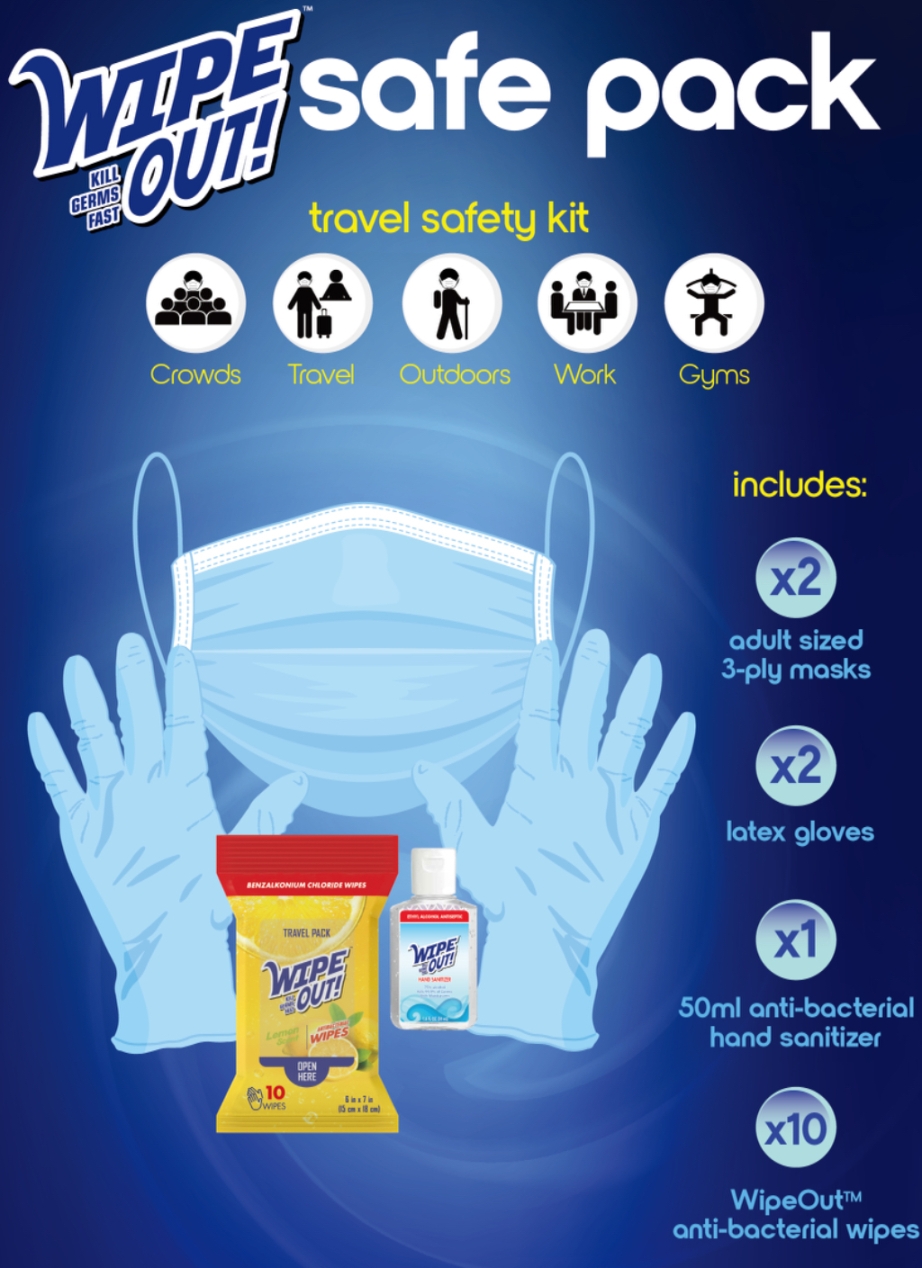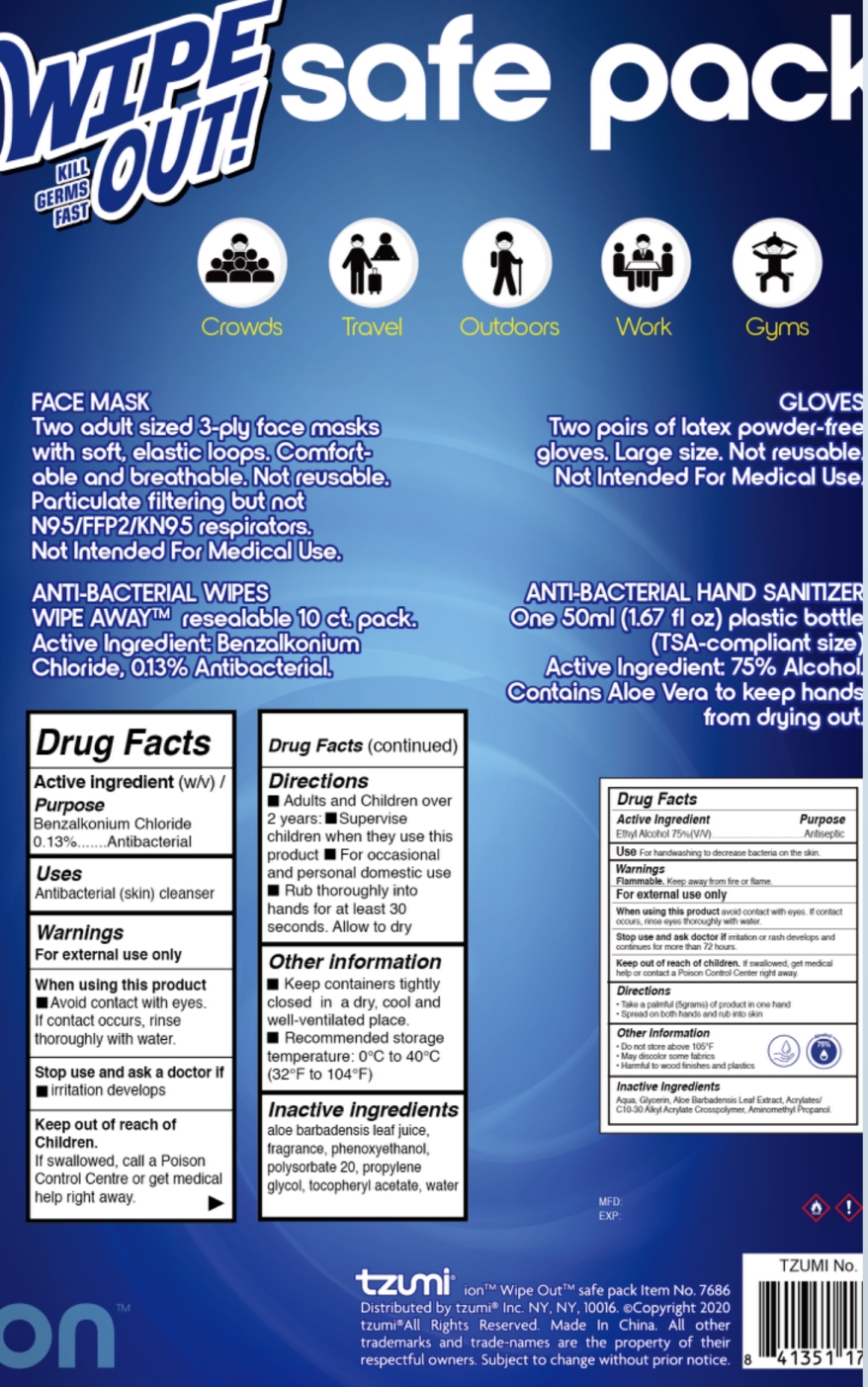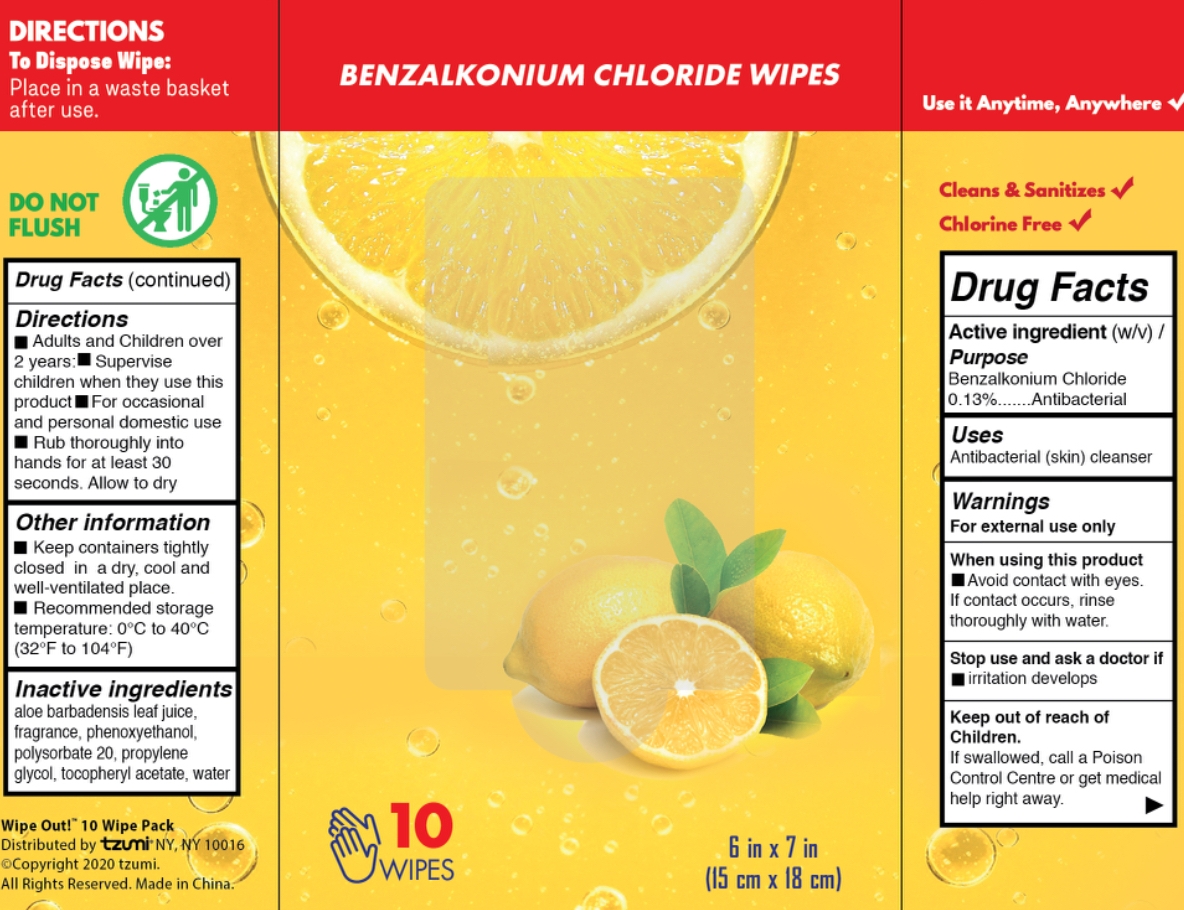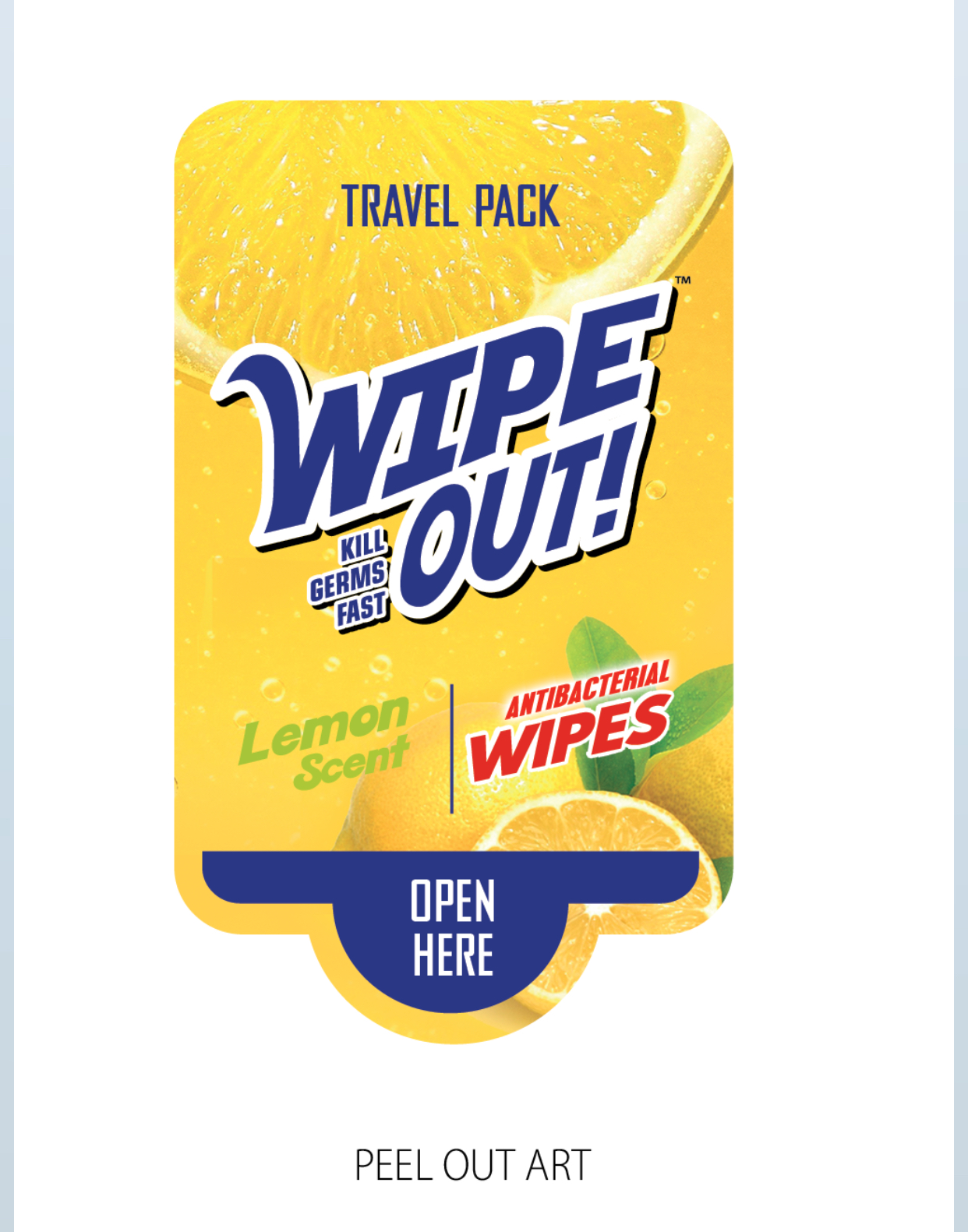 DRUG LABEL: WIPE OUT Safe Pack
NDC: 77878-014 | Form: KIT | Route: TOPICAL
Manufacturer: TZUMI INNOVATIONS LLC
Category: otc | Type: HUMAN OTC DRUG LABEL
Date: 20210115

ACTIVE INGREDIENTS: ALCOHOL 75 mL/100 mL; BENZALKONIUM CHLORIDE 6.8 mg/1 1
INACTIVE INGREDIENTS: WATER; GLYCERIN; ALOE VERA LEAF; AMINOMETHYLPROPANOL; WATER; ALOE VERA LEAF; PROPYLENE GLYCOL; POLYSORBATE 20; PHENOXYETHANOL; .ALPHA.-TOCOPHEROL ACETATE

77878-012, 013, 014, Wipe Out! Safe Pack (style# 7686HD)

WIPE OUT Hand Sanitizer with Moisturizers

Active Ingredient

Ethyl Alcohol 75%

Purpose

Antiseptic

Use

■ To decrease bacteria on the skin

WARNINGS

For external use only

Flammable. Keep away from fire or flame

When using this product, avoid contact with eyes
If contact occurs, rinse eyes thoroughly with water

Stop Use

Stop use and ask a doctor if irritation or rash develops and continues for more than 72 hours

Keep out of reach of children. If swallowed, get medical help or contact a poison control center right away

Directions

Take a palmful of product in one hand, spread on both hands and rub into skin

Other information

Do not store above 105F

May discolor some fabrics

Harmful to wood finishes and plastics

Inactive ingredients

Water, Glycerin, Aloe Barbadensis Leaf Extract, AMINOMETHYL PROPANOL, ACRYLATES/C10-30 ALKYL ACRYLATE
CROSSPOLYMER

WIPE OUT Antibacterial Wipes Travel Pack Lemon Scent

Active Ingredient

Benzalkonium Chloride 0.13%

Purpose

Antibacterial

Uses

Decreases bacteria and germs on the skin that could cause disease

Warnings

For external use only

When using this product keep out of eyes. In case of contact with eyes, flush thoroughly with water.

Avoid contact with broken skin

Stop Use

Stop use and ask a doctor if irritation and redness develop, condition persists for more than 72 hours

Keep out of reach of children. If swallowed, get medical help or contact a Poison Control Center immediately

Directions

Wet hands thoroughly with product and allow to dry without wiping

For children under 6, use only under adult supervision

Not recommended for infants

Other Information

Keep containers tightly closed in a dry, cool and well ventilated place
Recommended storage temperature: 32F to 104F (0C to 40C)

Inactive Ingredients

Aloe Barbadensis Leaf Juice, Fragrance, Water, Phenoxyethanol, Polysorbate 20, Propylene Glycol, Tocopheryl Acetate